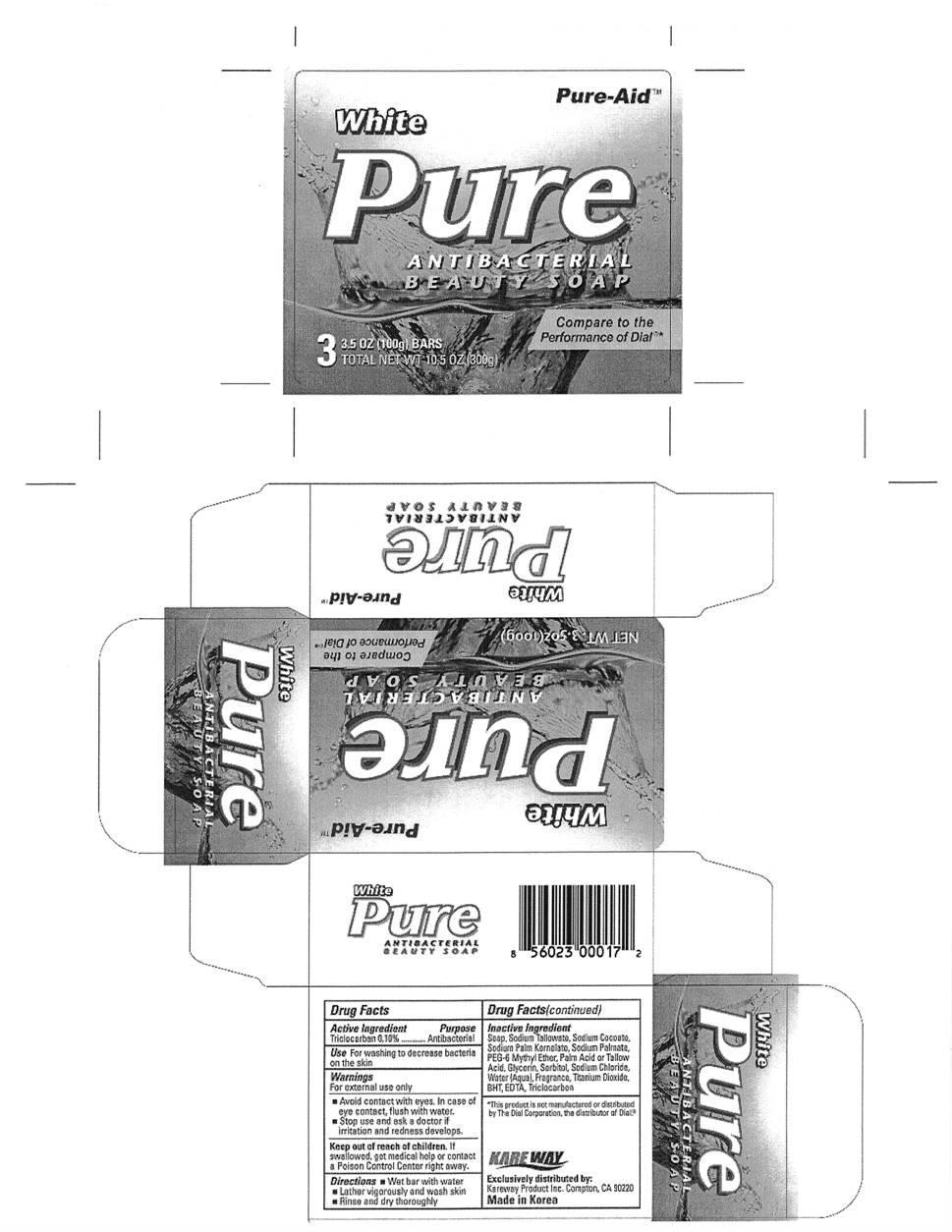 DRUG LABEL: Antibacterial Beauty
NDC: 67510-0017 | Form: SOAP
Manufacturer: Kareway Product, Inc.
Category: otc | Type: HUMAN OTC DRUG LABEL
Date: 20101001

ACTIVE INGREDIENTS: TRICLOCARBAN .1 g/100 g
INACTIVE INGREDIENTS: COCAMIDOPROPYL BETAINE; SODIUM CHLORIDE; SODIUM COCOYL ISETHIONATE; SODIUM PALMITATE; SODIUM PALM KERNELATE; STEARIC ACID; EDETATE SODIUM; TITANIUM DIOXIDE; TRICLOCARBAN; ETIDRONATE TETRASODIUM; BUTYLATED HYDROXYTOLUENE; WATER

Drug Facts

Active Ingredient

Triclocarban 0.10%

Purpose

Antibacterial

Use

For washing to decrease bacteria on the skin

Warnings

For external use only

- Avoid contact with eyes. In case of eye contact, flush with water.
- Stop use and ask a doctor if irritation and redness develops.

Keep out of reach of children.

If swallowed, get medical help or contact a Poison Control Center right away.

Directions

- Wet bar with water
- Lather vigorously and wash skin
- Rinse and dry thoroghly

Inactive Ingredient

BHT, cocamidopropyl betaine, fragrance, sodium chloride, sodium cocoyl isethionate, sodium palmitate, sodium palm kernelate, stearic acid, tetrasodium EDTA, titanium dioxide, triclocarban, trisodium etidronate, water

Package label

Pure Beauty Antibacterial White